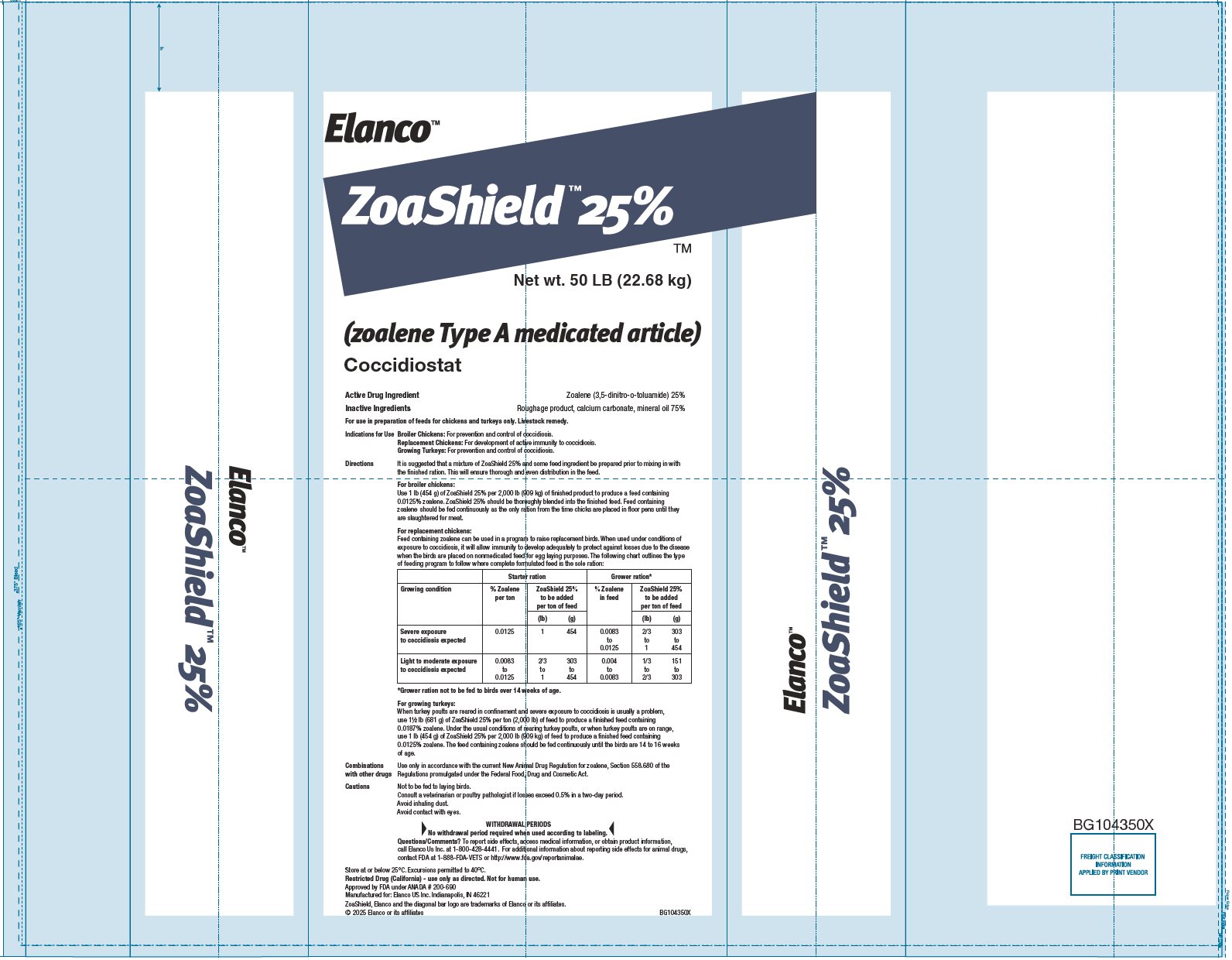 DRUG LABEL: ZoaShield
NDC: 58198-7636 | Form: GRANULE
Manufacturer: Elanco US Inc.
Category: animal | Type: OTC TYPE A MEDICATED ARTICLE ANIMAL DRUG LABEL
Date: 20260107

ACTIVE INGREDIENTS: DINITOLMIDE 5.67 kg/22.68 kg

Elanco™

ZoaShield™ 25%™

Net wt. 50 LB (22.68 kg)

(zoalene Type A medicated article)

Coccidiostat

Active Drug Ingredient

Zoalene (3,5-dinitro-o-toluamide) 25%

Inactive Ingredients

Roughage product, calcium carbonate, mineral oil 75%

WARNINGS

For use in preparation of feeds for chickens and turkeys only. Livestock remedy.

Indications for Use

Broiler Chickens: For prevention and control of coccidiosis.

Replacement Chickens: For development of active immunity to coccidiosis.

Growing Turkeys: For prevention and control of coccidiosis.

Directions

It is suggested that a mixture of ZoaShield 25% and some feed ingredient be prepared prior to mixing in with the finished ration. This will ensure thorough and even distribution in the feed.

For broiler chickens:

Use 1 lb (454 g) of ZoaShield 25% per 2,000 lb (909 kg) of finished product to produce a feed containing 0.0125% zoalene. ZoaShield 25% should be thoroughly blended into the finished feed. Feed containing zoalene should be fed continuously as the only ration from the time chicks are placed in floor pens until they are slaughtered for meat.

For replacement chickens:

Feed containing zoalene can be used in a program to raise replacement birds. When used under conditions of exposure to coccidiosis, it will allow immunity to develop adequately to protect against losses due to the disease when the birds are placed on nonmedicated feed for egg laying purposes. The following chart outlines the type of feeding program to follow where complete formulated feed is the sole ration:

 |  | Starter ration |  | Grower ration*
Growing condition | % Zoalene per ton | ZoaShield 25% to be added per ton of feed |  | % Zoalene in feed | ZoaShield 25% to be added per ton of feed
Growing condition | % Zoalene per ton | (lb) | (g) | % Zoalene in feed | (lb) | (g)
Severe exposure to coccidiosis expected | 0.0125 | 1 | 454 | 0.0083 to 0.0125 | 2/3 to 1 | 303 to 454
Light to moderate exposure to coccidiosis expected | 0.0083 to 0.0125 | 2/3 to 1 | 303 to 454 | 0.004 to 0.0083 | 1/3 to 2/3 | 151 to 303
*Grower ration not to be fed to birds over 14 weeks of age.

For growing turkeys:

When turkey poults are reared in confinement and severe exposure to coccidiosis is usually a problem, use 1½ lb (681 g) of ZoaShield 25% per ton (2,000 lb) of feed to produce a finished feed containing 0.0187% zoalene. Under the usual conditions of rearing turkey poults, or when turkey poults are on range, use 1 lb (454 g) of ZoaShield 25% per 2,000 lb (909 kg) of feed to produce a finished feed containing 0.0125% zoalene. The feed containing zoalene should be fed continuously until the birds are 14 to 16 weeks of age.

Combinations with other drugs

Use only in accordance with the current New Animal Drug Regulation for zoalene, Section 558.680 of the Regulations promulgated under the Federal Food, Drug and Cosmetic Act.

Cautions

Not to be fed to laying birds.

Consult a veterinarian or poultry pathologist if losses exceed 0.5% in a two-day period.

Avoid inhaling dust.

Avoid contact with eyes.

WITHDRAWAL PERIODS

No withdrawal period required when used according to labeling.

Questions/Comments?

To report side effects, access medical information, or obtain product information, call Elanco US Inc. at 1-800-428-4441.

For additional information about reporting side effects for animal drugs, contact FDA at 1-888-FDA-VETS or http://www.fda.gov/reportanimalae.

STORAGE AND HANDLING

Store at or below 25°C. Excursions permitted to 40°C.

Restricted Drug (California) - use only as directed. Not for human use.

Approved by FDA under ANADA # 200-690

Manufactured for: Elanco US Inc. Indianapolis, IN 46221

ZoaShield, Elanco and the diagonal bar logo are trademarks of Elanco or its affiliates. © 2025 Elanco or its affiliates

YL104350X

Principal Display Panel - 50 lb Bag Label

Elanco™

ZoaShield™ 25%

™

Net wt. 50 LB (22.68 kg)

(zoalene Type A medicated article)

Coccidiostat